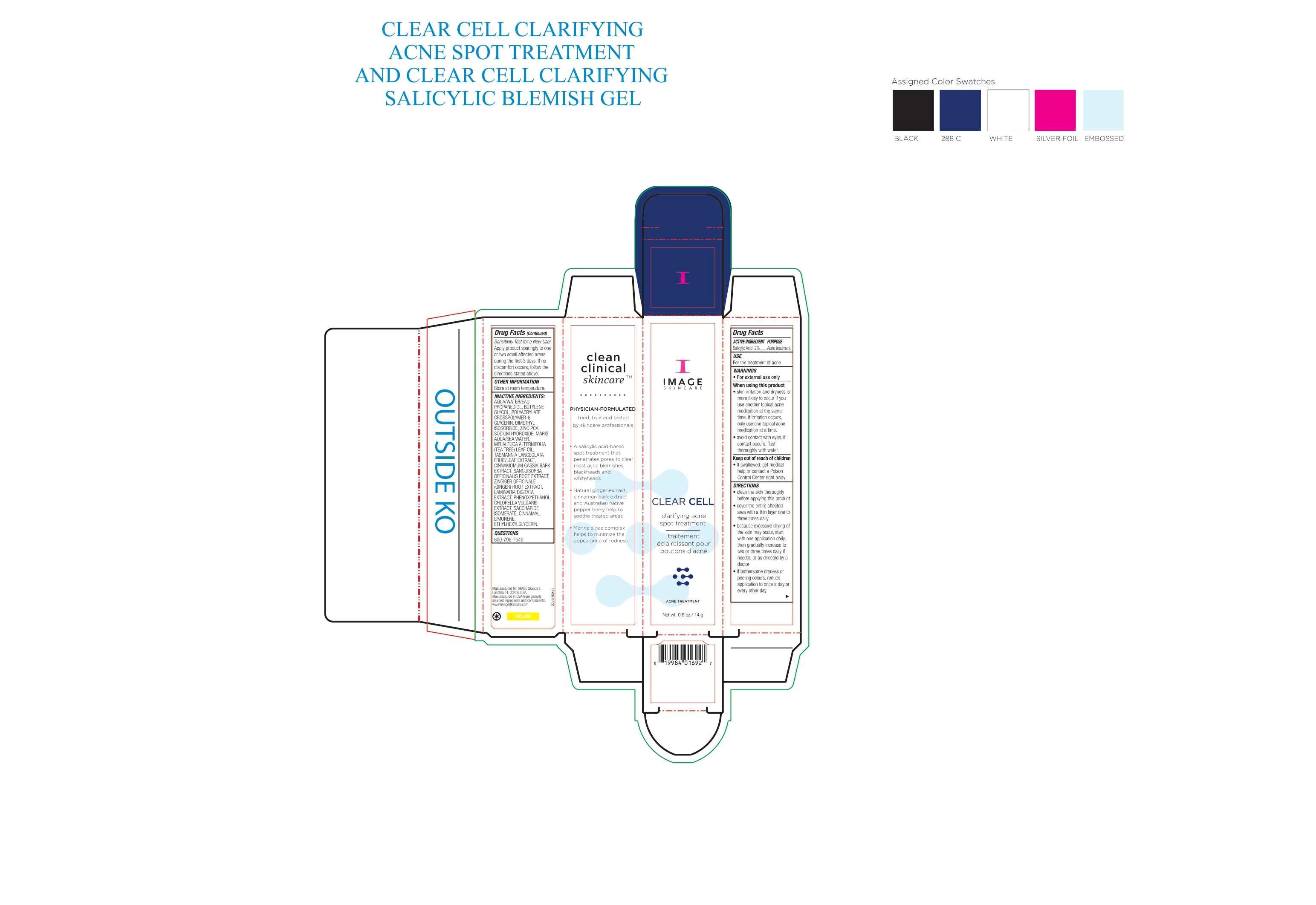 DRUG LABEL: Image Skincare Clear Cell Clarifying Acne Spot Treatment
NDC: 79458-002 | Form: GEL
Manufacturer: Natural Technology, LLC
Category: otc | Type: HUMAN OTC DRUG LABEL
Date: 20220317

ACTIVE INGREDIENTS: SALICYLIC ACID 20 g/1000 g
INACTIVE INGREDIENTS: GLYCERIN; CHLORELLA VULGARIS; SODIUM HYDROXIDE; PHENOXYETHANOL; TASMANNIA LANCEOLATA LEAF; WATER; AMMONIUM ACRYLOYLDIMETHYLTAURATE, DIMETHYLACRYLAMIDE, LAURYL METHACRYLATE AND LAURETH-4 METHACRYLATE COPOLYMER, TRIMETHYLOLPROPANE TRIACRYLATE CROSSLINKED (45000 MPA.S); TEA TREE OIL; TASMANNIA LANCEOLATA FRUIT; CHINESE CINNAMON; SANGUISORBA OFFICINALIS ROOT; GINGER; LAMINARIA DIGITATA; SACCHARIDE ISOMERATE; CINNAMALDEHYDE; ETHYLHEXYLGLYCERIN; PROPANEDIOL; ZINC PIDOLATE; LIMONENE, (+)-; BUTYLENE GLYCOL; DIMETHYL ISOSORBIDE; SODIUM CHLORIDE

Salicylic Acid 2%. Purpose: Acne Treatment

14g. NDC: 79458-002-00

Purpose: Acne Treatment

14 g. NDC: 79458-002-00

For external use only

14 g. NDC: 79458-002-00

- Skin irritation and dryness is more likely to occur if you use another topical acne medication at the same time. If irritation occurs, only use one topical acne medication at a time. - Avoid contact with eyes. If contact occurs, flush thoroughly with water.

14 g. NDC: 79458-002-00

If swallowed, get medical help or contact Poison Control Center right away.

14g. NDC: 79458-002-00

- Clean the skin thoroughly before applying this product - Cover the entire affected area with a thin layer one to three times daily - Because excessive drying of the skin may occur, start with one application daily, then gradually increase to two or three times daily if needed or as directed by a doctor - If bothersome dryness or peeling occurs, reduce application to once a day or every other day

14 g. NDC: 79458-002-00

Sensitivity Test for a New User. Apply product sparingly to one or two small affected areas during the first three days. If no discomfort occurs, follow the directions stated above.

14 g. NDC: 79458-002-00

Store at room temperature.

14 g. NDC: 79458-002-00

Aqua/Water/EAU, Propanediol, Butylene Glycol, Polyacrylate Crosspolymer-6, Glycerin, Dimethyl Isosorbide, Zinc PCA, Sodium Hydroxide, Maris Aqua/Sea Water, Melaleuca Alternifolia (Tea Tree) Leaf Oil, Tasmannia Lanceolata Fruit/Leaf Extract, Cinnamomum Cassia Bark Extract, Sanguisorba Officinalis Root Extract, Zingiber Officinale (Ginger) Root Extract, Laminaria Digitata Extract, Phenoxyethanol, Chlorella Vulgaris Extract, Saccharide Isomerate, Cinnamal, Limonene, Ethylhexylglycerin.

14 g. NDC: 79458-002-00

Clear Cell clarifying acne spot treatment

14g. NDC: 79458-002-00